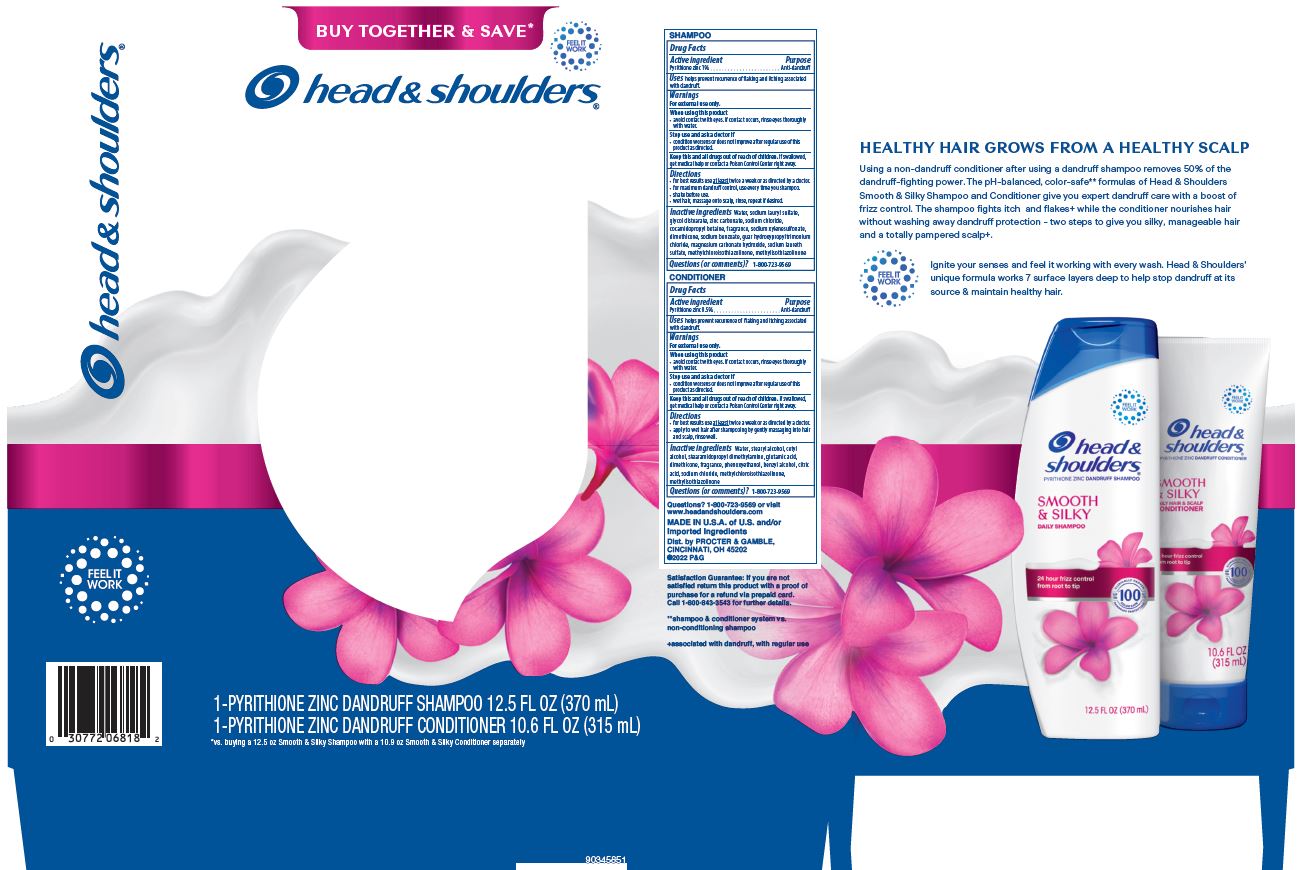 DRUG LABEL: Head and Shoulders Dual Pack
NDC: 69423-749 | Form: KIT | Route: TOPICAL
Manufacturer: The Procter & Gamble Manufacturing Company
Category: otc | Type: HUMAN OTC DRUG LABEL
Date: 20251231

ACTIVE INGREDIENTS: PYRITHIONE ZINC 1 g/100 mL; PYRITHIONE ZINC 0.5 g/100 mL
INACTIVE INGREDIENTS: COCAMIDOPROPYL BETAINE; GUAR HYDROXYPROPYLTRIMONIUM CHLORIDE (1.7 SUBSTITUENTS PER SACCHARIDE); WATER; SODIUM LAURETH-3 SULFATE; ZINC CARBONATE; GLYCOL DISTEARATE; SODIUM XYLENESULFONATE; DIMETHICONE; SODIUM CHLORIDE; SODIUM BENZOATE; MAGNESIUM CARBONATE HYDROXIDE; METHYLCHLOROISOTHIAZOLINONE; METHYLISOTHIAZOLINONE; SODIUM LAURYL SULFATE; SODIUM CHLORIDE; METHYLCHLOROISOTHIAZOLINONE; METHYLISOTHIAZOLINONE; WATER; STEARYL ALCOHOL; CETYL ALCOHOL; STEARAMIDOPROPYL DIMETHYLAMINE; DIMETHICONE; GLUTAMIC ACID; PHENOXYETHANOL; BENZYL ALCOHOL; CITRIC ACID MONOHYDRATE

Head and Shoulders® Dual Kit
Smooth and Silky

head &
shoulders
Smooth & Silky
pyrithione zinc dandruff shampoo

Drug Facts

Active ingredient

SHAMPOO: Pyrithione zinc 1%

Purpose

Anti-dandruff

Uses

helps prevent recurrence of flaking and itching associated with dandruff.

Warnings

For external use only.

When using this product

- avoid contact with eyes. If contact occurs, rinse eyes thoroughly with water.

Stop use and ask a doctor if

- condition worsens or does not improve after regular use of this product as directed.

KEEP OUT OF REACH OF CHILDREN

Keep this and all drugs out of reach of children.

If swallowed, get medical help or contact a Poison Control Center right away.

Directions

- for best results use at least twice a week or as directed by a doctor.
- for maximum dandruff control, use every time you shampoo.
- shake before use.
- wet hair, massage onto scalp, rinse, repeat if desired.

Inactive ingredients

Water, sodium lauryl sulfate, glycol distearate, zinc carbonate, sodium chloride, cocamidopropyl betaine, fragrance, sodium xylenesulfonate, dimethicone, sodium benzoate, guar hydroxypropyltrimonium chloride, magnesium carbonate hydroxide, sodium laureth sulfate, methylchloroisothiazolinone, methylisothiazolinone

Questions (or comments)?

1-800-723-9569

head &
shoulders
Smooth & Silky
pyrithione zinc dandruff conditioner

Drug Facts

Active ingredient

Pyrithione zinc 0.5%

Purpose

Anti-dandruff

Uses

helps prevent recurrence of flaking and itching associated with dandruff.

Warnings

For external use only.

When using this product

- avoid contact with eyes. If contact occurs, rinse eyes thoroughly with water.

Stop use and ask a doctor if

- condition worsens or does not improve after regular use of this product as directed.

KEEP OUT OF REACH OF CHILDREN

Keep this and all drugs out of reach of children.

If swallowed, get medical help or contact a Poison Control Center right away.

Directions

- for best results use at least twice a week or as directed by a doctor.
- apply to wet hair after shampooing by gently massaging into hair and scalp, rinse well.

Inactive ingredients

Water, stearyl alcohol, cetyl alcohol, stearamidopropyl dimethylamine, glutamic acid, dimethicone, fragrance, phenoxyethanol, benzyl alcohol, citric acid, sodium chloride, methylchloroisothiazolinone, methylisothiazolinone

Questions (or comments)?

1-800-723-9569

Dist. by PROCTER & GAMBLE,
CINCINNATI, OH 45202

PRINCIPAL DISPLAY PANEL - Kit Package

head &
shoulders®

pyrithione zinc dandruff shampoo

smooth & silky

FLAKE FREE.*
UP TO 100%
COLOR SAFE

12.5 FL OZ (370 mL)

head &
shoulders®

pyrithione zinc dandruff conditioner

smooth & silky

10.6 FL OZ (315 mL)